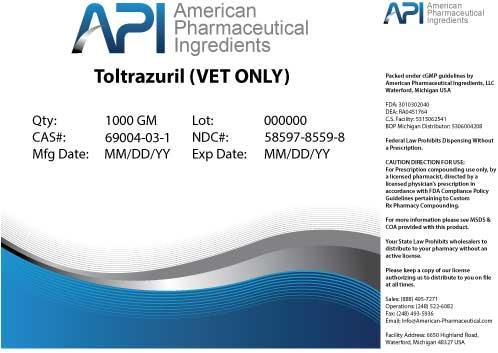 DRUG LABEL: Toltrazuril
NDC: 58597-8559 | Form: POWDER
Manufacturer: AMERICAN PHARMACEUTICAL INGREDIENTS LLC
Category: other | Type: BULK INGREDIENT
Date: 20140502

ACTIVE INGREDIENTS: Toltrazuril 1 g/1 g

Toltrazuril